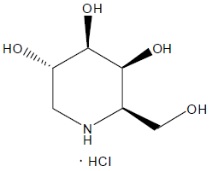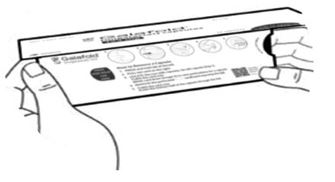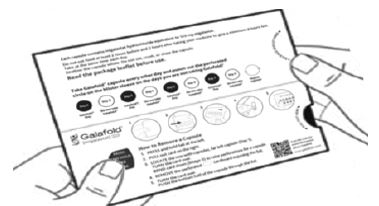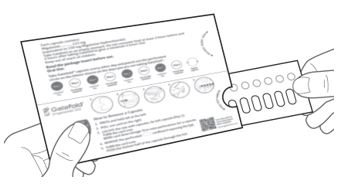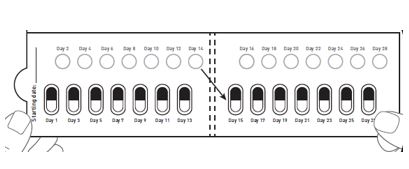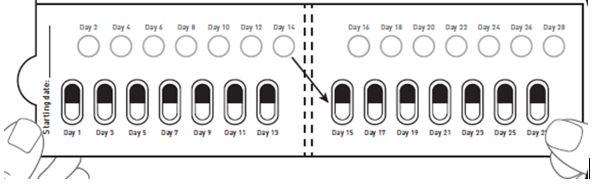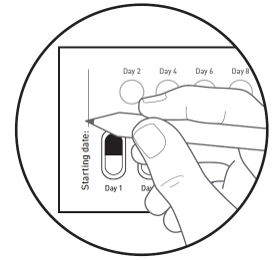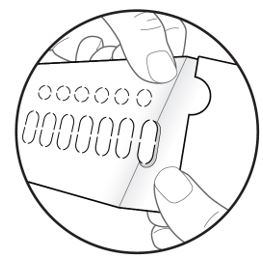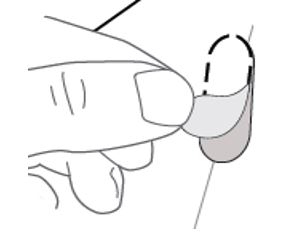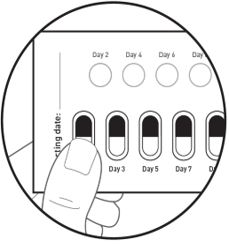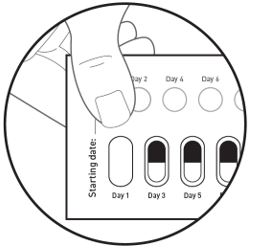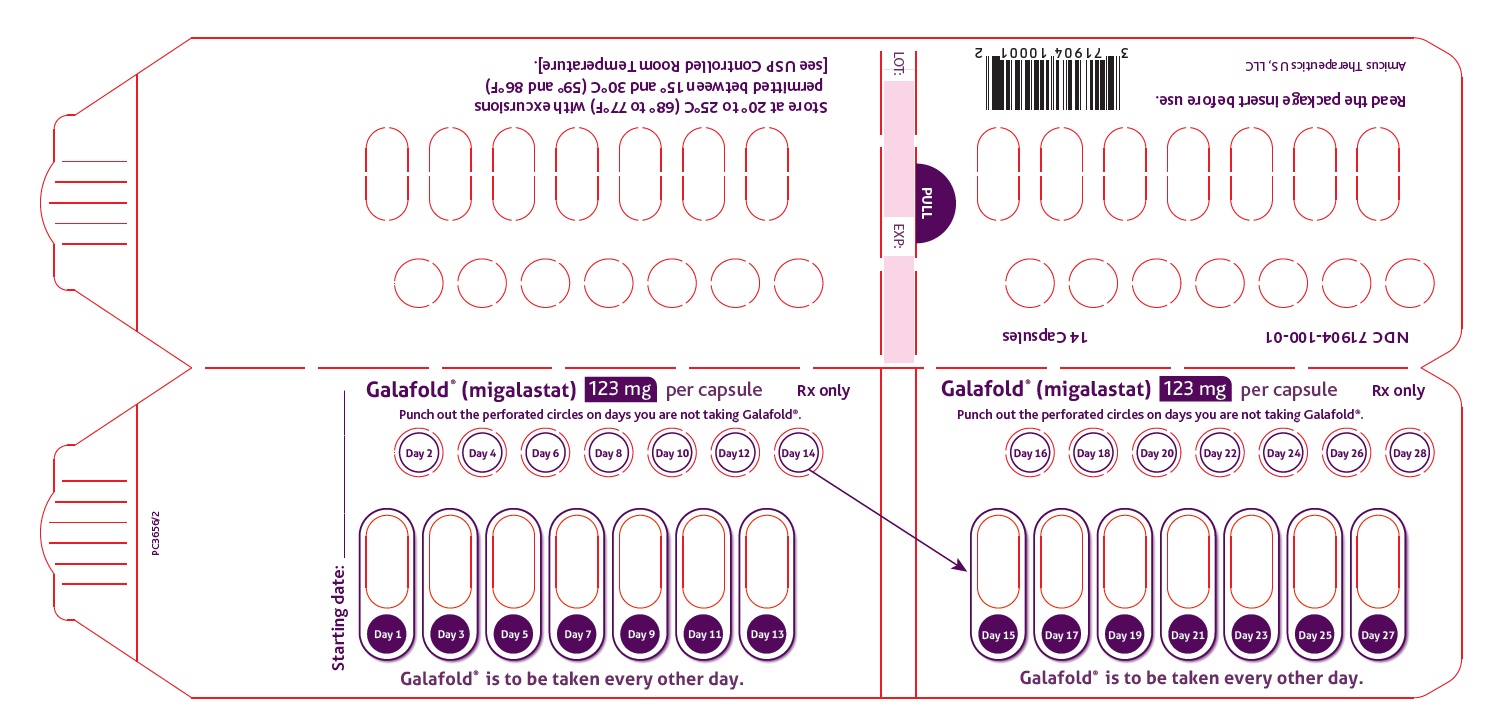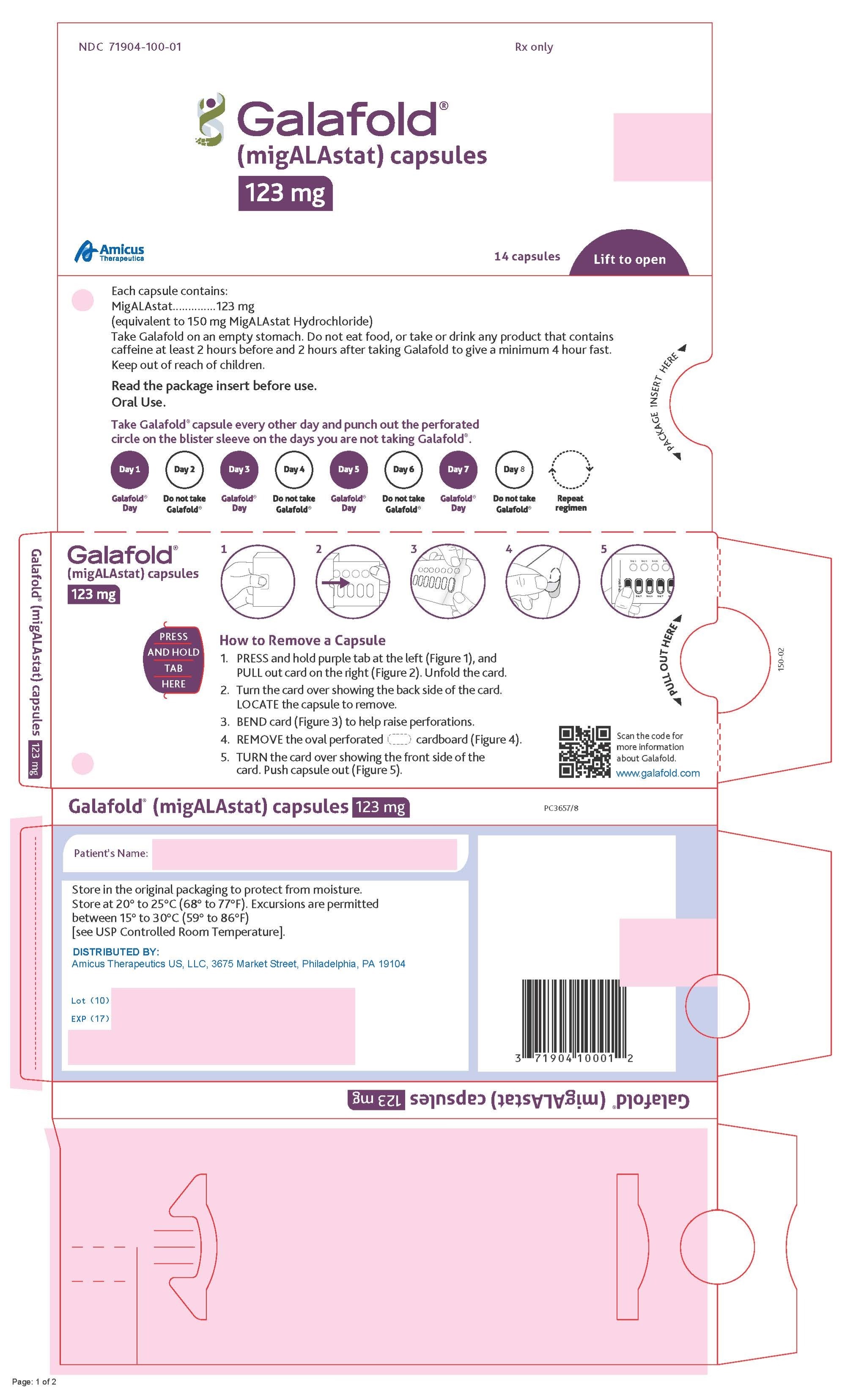 DRUG LABEL: Galafold
NDC: 71904-100 | Form: CAPSULE
Manufacturer: Amicus Therapeutics US, LLC
Category: prescription | Type: HUMAN PRESCRIPTION DRUG LABEL
Date: 20250828

ACTIVE INGREDIENTS: MIGALASTAT HYDROCHLORIDE 123 mg/1 1
INACTIVE INGREDIENTS: SHELLAC; MAGNESIUM STEARATE; STARCH, CORN; GELATIN; FD&C BLUE NO. 2; TITANIUM DIOXIDE; FERROSOFERRIC OXIDE; POTASSIUM HYDROXIDE

HIGHLIGHTS OF PRESCRIBING INFORMATION

These highlights do not include all the information needed to use GALAFOLD safely and effectively. See full prescribing information for GALAFOLD.
GALAFOLD® (migalastat) capsules, for oral use
Initial U.S. Approval: 2018

1 INDICATIONS AND USAGE

GALAFOLD is an alpha-galactosidase A (alpha-Gal A) pharmacological chaperone indicated for the treatment of adults with a confirmed diagnosis of Fabry disease and an amenable galactosidase alpha gene (GLA) variant based on in vitro assay data. (1, 12.1)

This indication is approved under accelerated approval based on reduction in kidney interstitial capillary cell globotriaosylceramide (KIC GL-3) substrate. Continued approval for this indication may be contingent upon verification and description of clinical benefit in confirmatory trials. (1)

2 DOSAGE AND ADMINISTRATION

- Select adults with confirmed Fabry disease who have an amenable GLA variant for treatment with GALAFOLD. (2.1)
- Treatment is indicated for patients with an amenable GLA variant that is interpreted by a clinical genetics professional as causing Fabry disease (pathogenic, likely pathogenic) in the clinical context of the patient. Consultation with a clinical genetics professional is strongly recommended in cases where the amenable GLA variant is of uncertain clinical significance (VUS, variant of uncertain significance) or may be benign (not causing Fabry disease). (2.1, 12.1)
- The recommended dosage of GALAFOLD is 123 mg orally once every other day. Take GALAFOLD at the same time of day and do not take on consecutive days. Swallow capsule whole. Do not cut, crush, or chew the capsule. (2.2)
- Take GALAFOLD on an empty stomach. Do not consume food or caffeine at least 2 hours prior to and 2 hours after taking GALAFOLD to give a minimum 4 hour fast. (2.2)
- If the GALAFOLD dose is missed, take the missed dose if it is within 12 hours of the time that the dose should have been taken. If more than 12 hours have passed, take GALAFOLD at the next planned dosing day and time following the original every-other-day dosing schedule. (2.3)

3 DOSAGE FORMS AND STRENGTHS

Capsules: 123 mg migalastat. (3)

4 CONTRAINDICATIONS

None. (4)

6 ADVERSE REACTIONS

Most common adverse drug reactions ≥ 10% are: headache, nasopharyngitis, urinary tract infection, nausea, and pyrexia. (6.1)

To report SUSPECTED ADVERSE REACTIONS, contact Amicus Therapeutics at 1-877-4AMICUS or FDA at 1-800-FDA-1088 or www.fda.gov/medwatch.

7 DRUG INTERACTIONS

See Full Prescribing Information for clinically significant drug interactions. (7.1)

FULL PRESCRIBING INFORMATION

1 INDICATIONS AND USAGE

GALAFOLD is indicated for the treatment of adults with a confirmed diagnosis of Fabry disease and an amenable galactosidase alpha gene (GLA) variant based on in vitro assay data [see Dosage and Administration (2.1) and Clinical Pharmacology (12.1)].

This indication is approved under accelerated approval based on reduction in kidney interstitial capillary cell globotriaosylceramide (KIC GL-3) substrate [see Clinical Studies (14)]. Continued approval for this indication may be contingent upon verification and description of clinical benefit in confirmatory trials.

2 DOSAGE AND ADMINISTRATION

2.1 Patient Selection

Select adults with confirmed Fabry disease who have an amenable GLA variant for treatment with GALAFOLD [see Clinical Pharmacology (12.1)].

Treatment is indicated for patients with an amenable GLA variant that is interpreted by a clinical genetics professional as causing Fabry disease (pathogenic, likely pathogenic) in the clinical context of the patient. Consultation with a clinical genetics professional is strongly recommended in cases where the amenable GLA variant is of uncertain clinical significance (VUS, variant of uncertain significance) or may be benign (not causing Fabry disease).

2.2 Recommended Dosage and Administration

The recommended dosage of GALAFOLD is 123 mg orally once every other day.

Take GALAFOLD at the same time of day and do not take on consecutive days.

Swallow capsule whole. Do not cut, crush, or chew the capsule.

Take GALAFOLD on an empty stomach. Do not consume food or caffeine at least 2 hours prior to and 2 hours after taking GALAFOLD to give a minimum 4 hour fast [see Clinical Pharmacology (12.3)].

Water (plain, flavored, or sweetened), fruit juices without pulp, and caffeine-free carbonated beverages can be consumed during the fasting period.

2.3 Recommendations for a Missed Dose

If the GALAFOLD dose is missed, take the missed dose if it is within 12 hours of the time that the dose should have been taken. If more than 12 hours have passed, take GALAFOLD at the next planned dosing day and time following the original every-other-day dosing schedule.

3 DOSAGE FORMS AND STRENGTHS

Capsules: 123 mg of migalastat in a size “2” capsule with an opaque blue cap and opaque white body with “A1001” printed in black, containing white to pale brown powder.

4 CONTRAINDICATIONS

None.

6 ADVERSE REACTIONS

6.1 Clinical Trials Experience

Because clinical trials are conducted under widely varying conditions, adverse reaction rates observed in the clinical trials of a drug cannot be directly compared to rates in the clinical trials of another drug and may not reflect the rates observed in practice.

In clinical trials, 139 patients with Fabry disease (79 females, 60 males, 92% Caucasian, ages 16 to 72 years), who were naïve to GALAFOLD or previously treated with enzyme replacement therapy, were exposed to at least one dose of GALAFOLD. Of the 139 patients, 127 patients were exposed to GALAFOLD 123 mg every other day for 6 months and 123 patients were exposed for greater than one year. The clinical trials included one randomized, double-blind, placebo-controlled clinical trial of 6 months duration followed by a 6-month open-label treatment phase (Study 1) [see Clinical Studies (14)]. A second trial was a randomized, open-label, active-controlled clinical trial of 18 months duration in patients with Fabry disease receiving enzyme replacement therapy who were randomized to either switch to GALAFOLD or continue enzyme replacement therapy (Study 2; NCT01218659). In addition, there were two open-label, long-term extension trials.

The most common adverse reactions reported with GALAFOLD (≥ 10%) during the 6-month placebo-controlled, double-blind phase of Study 1 were headache, nasopharyngitis, urinary tract infection, nausea, and pyrexia.

Table 1 shows adverse reactions that occurred in at least 5% of patients treated with GALAFOLD during the 6-month placebo-controlled, double-blind phase of Study 1.

Table 1: Adverse Reactions* in Patients with Fabry Disease (Study 1)
Adverse Reaction | GALAFOLD % (N = 34) | Placebo % (N = 33)
Headache | 35% | 21%
Nasopharyngitis | 18% | 6%
Urinary tract infection** | 15% | 0
Nausea | 12% | 6%
Pyrexia | 12% | 3%
Abdominal pain | 9% | 3%
Back pain | 9% | 0
Cough | 9% | 0
Diarrhea | 9% | 3%
Epistaxis | 9% | 3%
* Adverse reactions were those that occurred in at least 5% of patients treated with GALAFOLD.
** Included urinary tract infection, cystitis, and kidney infection

Adverse reactions that occurred in > 5% of patients who received GALAFOLD in the 6-month open-label treatment phase of Study 1, in Study 2, and in the long-term extension trials (N = 115, mean duration of treatment 2.7 years) included those in Table 1 with the addition of vomiting.

6.2 Postmarketing Experience

The following adverse reaction has been identified during post-approval use of GALAFOLD. Because this reaction is reported voluntarily from a population of uncertain size, it is not always possible to reliably estimate its frequency or establish a causal relationship to drug exposure.

General disorder: angioedema

7 DRUG INTERACTIONS

7.1 Effect of Other Drugs on GALAFOLD

Co-administration of GALAFOLD with caffeine decreases migalastat AUC and Cmax [see Clinical Pharmacology (12.3)] which may reduce GALAFOLD efficacy. Avoid co-administration of GALAFOLD with caffeine at least 2 hours before and 2 hours after taking GALAFOLD [see Dosage and Administration (2.2)].

8 USE IN SPECIFIC POPULATIONS

8.1 Pregnancy

Risk Summary

There were three pregnant women with Fabry disease exposed to GALAFOLD in clinical trials. As such, the available data are not sufficient to assess drug associated risks of major birth defects, miscarriage, or adverse maternal or fetal outcomes. In animal reproduction studies, no adverse developmental effects were observed (see Data).

The background risk for major birth defects and miscarriage for the indicated population is unknown. All pregnancies have a background risk of birth defects, loss, or other adverse outcomes. In the U.S. general population, the background risk of major birth defects and miscarriage in clinically recognized pregnancies is 2% to 4% and 15% to 20%, respectively.

There is a study that collects data on pregnant women with Fabry disease, either exposed or unexposed to GALAFOLD. Healthcare providers are encouraged to register patients or obtain additional information by contacting the Pregnancy Coordinating Center at 1-888-239-0758, emailing fabrypregnancy@ubc.com, or visiting www.fabrypregnancyregistry.com.

Data

Animal Data

No adverse developmental effects were observed with oral administration of migalastat to pregnant rats and rabbits during organogenesis at doses up to 26 and 54 times, respectively, the recommended dose based on AUC. No effects on post-natal development were observed following oral administration of up to 500 mg/kg migalastat twice daily to pregnant rats (16 times the recommended dose based on AUC) during organogenesis and through lactation.

8.2 Lactation

Risk Summary

There are no data on the presence of migalastat in human milk, the effects on the breastfed infant, or the effects on milk production. Migalastat is present in the milk of lactating rats (see Data). When a drug is present in animal milk, it is likely that the drug will be present in human milk. The developmental and health benefits of breastfeeding should be considered along with the mother’s clinical need for GALAFOLD and any potential adverse effects on the breastfed infant from GALAFOLD or from the underlying maternal condition.

There is a study that collects data on effects of GALAFOLD on lactation for women with Fabry disease and their neonates and infants up to 1 year of age who are exposed through breast milk. Healthcare providers are encouraged to register patients or obtain additional information by contacting the Pregnancy Coordinating Center at 1-888-239-0758, email fabrypregnancy@ubc.com, or visit www.fabrypregnancyregistry.com.

Data

Animal Data

Migalastat concentrations in milk from rats following oral administration of up to 500 mg/kg twice daily (approximately 16 times the recommended human dose based on AUC) was approximately 2.5 times higher than levels in the rat maternal plasma at 4 hours post-dose. The concentration of migalastat in plasma from pups was approximately 11 times lower than the maternal plasma concentrations at 1-hour post-dose.

8.3 Females and Males of Reproductive Potential

Infertility

The effects of GALAFOLD on fertility in humans have not been studied. Transient and fully reversible infertility in male rats was associated with migalastat treatment at a systemic exposure (AUC) equivalent to the human exposure at the recommended dose. Complete reversibility was seen at 4 weeks after the termination of treatment. Migalastat did not affect fertility in female rats [see Nonclinical Toxicology (13.1)].

8.4 Pediatric Use

The safety and effectiveness of GALAFOLD have not been established in pediatric patients.

8.5 Geriatric Use

Clinical trials of GALAFOLD did not include sufficient numbers of patients 65 years of age and older to determine whether they respond differently from younger adult patients.

8.6 Renal Impairment

Migalastat is substantially excreted by the kidneys. Systemic exposure was significantly increased in subjects with severe renal impairment (eGFR less than 30 mL/min/1.73 m^2).

GALAFOLD has not been studied in patients with Fabry disease who have an eGFR less than 30 mL/min/1.73 m^2. GALAFOLD is not recommended for use in patients with severe renal impairment or end-stage renal disease requiring dialysis.

No dosage adjustment is required in patients with mild to moderate renal impairment (eGFR at least 30 mL/min/1.73 m^2 and above) [see Clinical Pharmacology (12.3)].

11 DESCRIPTION

Migalastat, an alpha-galactosidase A (alpha-Gal A) pharmacological chaperone, is a low molecular weight iminosugar and an analogue of the terminal galactose of globotriaosylceramide (GL-3).

Migalastat is present in the form of a hydrochloride salt in GALAFOLD. The chemical name for migalastat hydrochloride is (+)-(2R,3S,4R,5S)-2-(hydroxymethyl) piperidine-3,4,5-triol hydrochloride. Its molecular formula is C6H13NO4•HCl, molecular mass is 199.63 g/mol, and its chemical structure is depicted below.

Migalastat hydrochloride is a white to almost white crystalline solid. It is freely soluble in aqueous media within the pH range of 1.2 to 7.5.

GALAFOLD (migalastat) capsules for oral administration contain 123 mg of migalastat (equivalent to 150 mg migalastat hydrochloride) as a white to pale brown powder and are supplied in a size “2” hard gelatin capsule with an opaque blue cap and an opaque white body imprinted with “A1001” in black ink. The inactive ingredients are magnesium stearate and pregelatinized starch. Capsule shells consist of gelatin, indigotine - FD&C Blue 2, and titanium dioxide. The black ink consists of black iron oxide, potassium hydroxide, and shellac.

12 CLINICAL PHARMACOLOGY

12.1 Mechanism of Action

Migalastat is a pharmacological chaperone that reversibly binds to the active site of the alpha-galactosidase A (alpha-Gal A) protein (encoded by the galactosidase alpha gene, GLA), which is deficient in Fabry disease. This binding stabilizes alpha-Gal A allowing its trafficking from the endoplasmic reticulum into the lysosome where it exerts its action. In the lysosome, at a lower pH and at a higher concentration of relevant substrates, migalastat dissociates from alpha-Gal A allowing it to break down the glycosphingolipids globotriaosylceramide (GL-3) and globotriaosylsphingosine (lyso-Gb3). Certain GLA variants (mutations) causing Fabry disease result in the production of abnormally folded and less stable forms of the alpha-Gal A protein which, however, retain enzymatic activity. Those GLA variants, referred to as amenable variants, produce alpha-Gal A proteins that may be stabilized by migalastat thereby restoring their trafficking to lysosomes and their intralysosomal activity.

In Vitro Amenability Assay

In an in vitro assay (HEK-293 assay), Human Embryonic Kidney (HEK-293) cell lines were transfected with specific GLA variants which produced variant alpha-Gal A proteins. In the transfected cells, amenability of the GLA variants was assessed after a 5-day incubation with 10 micromol/L migalastat. A GLA variant was categorized as amenable if the resultant variant alpha-Gal A activity (measured in the cell lysates) met two criteria: 1) it showed a relative increase of at least 20% compared to the pre-treatment alpha-Gal A activity, and 2) it showed an absolute increase of at least 3% of the wild-type (normal) alpha-Gal A activity.

The in vitro assay did not evaluate trafficking of the variant alpha-Gal A proteins into the lysosome or the dissociation of migalastat from the variant alpha-Gal A proteins within the lysosome. Also, the in vitro assay did not test whether a GLA variant causes Fabry disease or not.

The GLA variants that are amenable to treatment with GALAFOLD, either based on the in vitro assay data or on the concept that synonymous nucleotide changes leading to the same variant alpha-Gal A protein as a confirmed amenable GLA variant are amenable without additional testing, are shown in Table 2. In patients with multiple identified variants, the amenability assessment of each independent variant may not reflect the overall amenability classification of the combination of variants. The specific variant combination must be present within Table 2 (eg, c.[164A>T; 170A>T]) and on a single chromosome (males and females) to be considered amenable to treatment with GALAFOLD. When multiple variants are identified in a female, it is recommended to consult a clinical genetics professional to determine whether the variants are on a single GLA allele.

Inclusion of GLA variants in this table does not reflect interpretation of their clinical significance in Fabry disease. Whether a certain amenable GLA variant in a patient with Fabry disease is disease-causing or not should be determined by the prescribing physician (in consultation with a clinical genetics professional, if needed) prior to treatment initiation. Consultation with a clinical genetics professional is strongly recommended in cases where the amenable GLA variant is of uncertain clinical significance (VUS, variant of uncertain significance) or may be benign (not causing Fabry disease).

If a GLA variant does not appear in Table 2, it is either non-amenable (if tested) or has not been tested for in vitro amenability. For further information, please contact Amicus Medical Information at 1-877-4AMICUS or medinfousa@amicusrx.com.

Table 2: Amenable GLA Variants Based on the In Vitro Assay
DNA Change (Long) | DNA Change (Short) | Protein Change (1-letter Code) | Protein Change (3-letter Code)
c.7C>G | c.C7G | p.(L3V) | p.(Leu3Val)
c.8T>C | c.T8C | p.(L3P) | p.(Leu3Pro)
c.[11G>T; 620A>C]† | c.[G11T; A620C]† | p.[(R4M; Y207S)]† | p.[(Arg4Met; Tyr207Ser)]†
c.37G>A | c.G37A | p.(A13T) | p.(Ala13Thr)
c.37G>C | c.G37C | p.(A13P) | p.(Ala13Pro)
c.43G>A | c.G43A | p.(A15T) | p.(Ala15Thr)
c.44C>G | c.C44G | p.(A15G) | p.(Ala15Gly)
c.53T>G | c.T53G | p.(F18C) | p.(Phe18Cys)
c.58G>C | c.G58C | p.(A20P) | p.(Ala20Pro)
c.59C>A | c.C59A | p.(A20D) | p.(Ala20Asp)
c.65T>G | c.T65G | p.(V22G) | p.(Val22Gly)
c.[70T>A; 1255A>G]† | c.[T70A; A1255G]† | p.[(W24R; N419D)]† | p.[(Trp24Arg; Asn419Asp)]†
c.70T>A or c.70T>C‡ | c.T70A or c.T70C‡ | p.(W24R) | p.(Trp24Arg)
c.70T>G | c.T70G | p.(W24G) | p.(Trp24Gly)
c.72G>C or c.72G>T‡ | c.G72C or c.G72T‡ | p.(W24C) | p.(Trp24Cys)
c.95T>C | c.T95C | p.(L32P) | p.(Leu32Pro)
c.97G>C | c.G97C | p.(D33H) | p.(Asp33His)
c.97G>T | c.G97T | p.(D33Y) | p.(Asp33Tyr)
c.98A>G | c.A98G | p.(D33G) | p.(Asp33Gly)
c.100A>C | c.A100C | p.(N34H) | p.(Asn34His)
c.100A>G | c.A100G | p.(N34D) | p.(Asn34Asp)
c.101A>C | c.A101C | p.(N34T) | p.(Asn34Thr)
c.101A>G | c.A101G | p.(N34S) | p.(Asn34Ser)
c.102T>A or c.102T>G‡ | c.T102A or c.T102G‡ | p.(N34K) | p.(Asn34Lys)
c.103G>A or c.103G>C‡ | c.G103A or c.G103C‡ | p.(G35R) | p.(Gly35Arg)
c.104G>A | c.G104A | p.(G35E) | p.(Gly35Glu)
c.104G>T | c.G104T | p.(G35V) | p.(Gly35Val)
c.107T>C | c.T107C | p.(L36S) | p.(Leu36Ser)
c.107T>G | c.T107G | p.(L36W) | p.(Leu36Trp)
c.108G>C or c.108G>T‡ | c.G108C or c.G108T‡ | p.(L36F) | p.(Leu36Phe)
c.109G>A | c.G109A | p.(A37T) | p.(Ala37Thr)
c.109G>T | c.G109T | p.(A37S) | p.(Ala37Ser)
c.110C>T | c.C110T | p.(A37V) | p.(Ala37Val)
c.122C>T | c.C122T | p.(T41I) | p.(Thr41Ile)
c.124A>C or c.124A>T‡ | c.A124C or c.A124T‡ | p.(M42L) | p.(Met42Leu)
c.124A>G | c.A124G | p.(M42V) | p.(Met42Val)
c.125T>A | c.T125A | p.(M42K) | p.(Met42Lys)
c.125T>C | c.T125C | p.(M42T) | p.(Met42Thr)
c.125T>G | c.T125G | p.(M42R) | p.(Met42Arg)
c.126G>A or c.126G>C‡ or c.126G>T‡ | c.G126A or c.G126C‡ or c.G126T‡ | p.(M42I) | p.(Met42Ile)
c.137A>C | c.A137C | p.(H46P) | p.(His46Pro)
c.142G>C | c.G142C | p.(E48Q) | p.(Glu48Gln)
c.152T>A | c.T152A | p.(M51K) | p.(Met51Lys)
c.153G>A or c.153G>T‡ or c.153G>C‡ | c.G153A or c.G153T‡ or c.G153C‡ | p.(M51I) | p.(Met51Ile)
c.157_158delinsCT | c.157_158delinsCT | p.(N53L) | p.(Asn53Leu)
c.157A>G | c.A157G | p.(N53D) | p.(Asn53Asp)
c.160C>T | c.C160T | p.(L54F) | p.(Leu54Phe)
c.161T>C | c.T161C | p.(L54P) | p.(Leu54Pro)
c.164A>G | c.A164G | p.(D55G) | p.(Asp55Gly)
c.164A>T | c.A164T | p.(D55V) | p.(Asp55Val)
c.[164A>T; 170A>T]† | c.[A164T; A170T]† | p.[(D55V; Q57L)]† | p.[(Asp55Val; Gln57Leu)]†
c.167G>A | c.G167A | p.(C56Y) | p.(Cys56Tyr)
c.167G>T | c.G167T | p.(C56F) | p.(Cys56Phe)
c.170A>G | c.A170G | p.(Q57R) | p.(Gln57Arg)
c.170A>T | c.A170T | p.(Q57L) | p.(Gln57Leu)
c.175G>A | c.G175A | p.(E59K) | p.(Glu59Lys)
c.178C>A | c.C178A | p.(P60T) | p.(Pro60Thr)
c.178C>T | c.C178T | p.(P60S) | p.(Pro60Ser)
c.179C>T | c.C179T | p.(P60L) | p.(Pro60Leu)
c.196G>A | c.G196A | p.(E66K) | p.(Glu66Lys)
c.197A>G | c.A197G | p.(E66G) | p.(Glu66Gly)
c.207C>A or c.207C>G‡ | c.C207A or c.C207G‡ | p.(F69L) | p.(Phe69Leu)
c.214A>G | c.A214G | p.(M72V) | p.(Met72Val)
c.216G>A or c.216G>T‡ or c.216G>C‡ | c.G216A or c.G216T‡ or c.G216C‡ | p.(M72I) | p.(Met72Ile)
c.218C>T | c.C218T | p.(A73V) | p.(Ala73Val)
c.227T>C | c.T227C | p.(M76T) | p.(Met76Thr)
c.239G>A | c.G239A | p.(G80D) | p.(Gly80Asp)
c.239G>T | c.G239T | p.(G80V) | p.(Gly80Val)
c.247G>A | c.G247A | p.(D83N) | p.(Asp83Asn)
c.253G>A | c.G253A | p.(G85S) | p.(Gly85Ser)
c.253_254delinsAA | c.253_254delinsAA | p.(G85N) | p.(Gly85Asn)
c.253_255delinsATG | c.253_255delinsATG | p.(G85M) | p.(Gly85Met)
c.254G>A | c.G254A | p.(G85D) | p.(Gly85Asp)
c.261G>C or c.261G>T‡ | c.G261C or c.G261T‡ | p.(E87D) | p.(Glu87Asp)
c.263A>G | c.A263G | p.(Y88C) | p.(Tyr88Cys)
c.265C>T | c.C265T | p.(L89F) | p.(Leu89Phe)
c.272T>C | c.T272C | p.(I91T) | p.(Ile91Thr)
c.288G>A or c.288G>T‡ or c.288G>C‡ | c.G288A or c.G288T‡ or c.G288C‡ | p.(M96I) | p.(Met96Ile)
c.289G>C | c.G289C | p.(A97P) | p.(Ala97Pro)
c.290C>T | c.C290T | p.(A97V) | p.(Ala97Val)
c.305C>T | c.C305T | p.(S102L) | p.(Ser102Leu)
c.311G>T | c.G311T | p.(G104V) | p.(Gly104Val)
c.316C>T | c.C316T | p.(L106F) | p.(Leu106Phe)
c.320A>G | c.A320G | p.(Q107R) | p.(Gln107Arg)
c.322G>A | c.G322A | p.(A108T) | p.(Ala108Thr)
c.326A>G | c.A326G | p.(D109G) | p.(Asp109Gly)
c.334C>G | c.C334G | p.(R112G) | p.(Arg112Gly)
c.335G>A | c.G335A | p.(R112H) | p.(Arg112His)
c.335G>T | c.G335T | p.(R112L) | p.(Arg112Leu)
c.337T>A | c.T337A | p.(F113I) | p.(Phe113Ile)
c.337T>C or c.339T>A‡ or c.339T>G‡ | c.T337C or c.T339A‡ or c.T339G‡ | p.(F113L) | p.(Phe113Leu)
c.352C>T | c.C352T | p.(R118C) | p.(Arg118Cys)
c.361G>A | c.G361A | p.(A121T) | p.(Ala121Thr)
c.368A>G | c.A368G | p.(Y123C) | p.(Tyr123Cys)
c.373C>T | c.C373T | p.(H125Y) | p.(His125Tyr)
c.374A>T | c.A374T | p.(H125L) | p.(His125Leu)
c.376A>G | c.A376G | p.(S126G) | p.(Ser126Gly)
c.376A>T | c.A376T | p.(S126C) | p.(Ser126Cys)
c.383G>A | c.G383A | p.(G128E) | p.(Gly128Glu)
c.399T>G | c.T399G | p.(I133M) | p.(Ile133Met)
c.404C>T | c.C404T | p.(A135V) | p.(Ala135Val)
c.408T>A or c.408T>G‡ | c.T408A or c.T408G‡ | p.(D136E) | p.(Asp136Glu)
c.416A>G | c.A416G | p.(N139S) | p.(Asn139Ser)
c.419A>C | c.A419C | p.(K140T) | p.(Lys140Thr)
c.427G>A | c.G427A | p.(A143T) | p.(Ala143Thr)
c.431G>A | c.G431A | p.(G144D) | p.(Gly144Asp)
c.431G>T | c.G431T | p.(G144V) | p.(Gly144Val)
c.434T>C | c.T434C | p.(F145S) | p.(Phe145Ser)
c.436C>T | c.C436T | p.(P146S) | p.(Pro146Ser)
c.437C>G | c.C437G | p.(P146R) | p.(Pro146Arg)
c.454T>C | c.T454C | p.(Y152H) | p.(Tyr152His)
c.454T>G | c.T454G | p.(Y152D) | p.(Tyr152Asp)
c.455A>G | c.A455G | p.(Y152C) | p.(Tyr152Cys)
c.465T>A or c.465T>G‡ | c.T465A or c.T465G‡ | p.(D155E) | p.(Asp155Glu)
c.466G>A | c.G466A | p.(A156T) | p.(Ala156Thr)
c.466G>T | c.G466T | p.(A156S) | p.(Ala156Ser)
c.467C>T | c.C467T | p.(A156V) | p.(Ala156Val)
c.471G>C or c.471G>T‡ | c.G471C or c.G471T‡ | p.(Q157H) | p.(Gln157His)
c.484T>G | c.T484G | p.(W162G) | p.(Trp162Gly)
c.493G>C | c.G493C | p.(D165H) | p.(Asp165His)
c.494A>G | c.A494G | p.(D165G) | p.(Asp165Gly)
c.496_497delinsTC | c.496_497delinsTC | p.(L166S) | p.(Leu166Ser)
c.496C>G | c.C496G | p.(L166V) | p.(Leu166Val)
c.496_497delinsGG | c.496_497delinsGG | p.(L166G) | p.(Leu166Gly)
c.499C>G | c.C499G | p.(L167V) | p.(Leu167Val)
c.506T>C | c.T506C | p.(F169S) | p.(Phe169Ser)
c.511G>A | c.G511A | p.(G171S) | p.(Gly171Ser)
c.520T>C | c.T520C | p.(C174R) | p.(Cys174Arg)
c.520T>G | c.T520G | p.(C174G) | p.(Cys174Gly)
c.525C>G or c.525C>A‡ | c.C525G or c.C525A‡ | p.(D175E) | p.(Asp175Glu)
c.539T>G | c.T539G | p.(L180W) | p.(Leu180Trp)
c.540G>T or c.540G>C‡ | c.G540T or c.G540C‡ | p.(L180F) | p.(Leu180Phe)
c.548G>A | c.G548A | p.(G183D) | p.(Gly183Asp)
c.548G>C | c.G548C | p.(G183A) | p.(Gly183Ala)
c.550T>A | c.T550A | p.(Y184N) | p.(Tyr184Asn)
c.551A>C | c.A551C | p.(Y184S) | p.(Tyr184Ser)
c.551A>G | c.A551G | p.(Y184C) | p.(Tyr184Cys)
c.553A>G | c.A553G | p.(K185E) | p.(Lys185Glu)
c.559_564dup | c.559_564dup | p.(M187_S188dup) | p.(Met187_Ser188dup)
c.559A>G | c.A559G | p.(M187V) | p.(Met187Val)
c.560T>C | c.T560C | p.(M187T) | p.(Met187Thr)
c.561G>A or c.561G>T‡ or c.561G>C‡ | c.G561A or c.G561T‡ or c.G561C‡ | p.(M187I) | p.(Met187Ile)
c.567G>C or c.567G>T‡ | c.G567C or c.G567T‡ | p.(L189F) | p.(Leu189Phe)
c.572T>A | c.T572A | p.(L191Q) | p.(Leu191Gln)
c.581C>T | c.C581T | p.(T194I) | p.(Thr194Ile)
c.584G>T | c.G584T | p.(G195V) | p.(Gly195Val)
c.586A>G | c.A586G | p.(R196G) | p.(Arg196Gly)
c.593T>C | c.T593C | p.(I198T) | p.(Ile198Thr)
c.595G>A | c.G595A | p.(V199M) | p.(Val199Met)
c.596T>C | c.T596C | p.(V199A) | p.(Val199Ala)
c.596T>G | c.T596G | p.(V199G) | p.(Val199Gly)
c.599A>G | c.A599G | p.(Y200C) | p.(Tyr200Cys)
c.602C>A | c.C602A | p.(S201Y) | p.(Ser201Tyr)
c.602C>T | c.C602T | p.(S201F) | p.(Ser201Phe)
c.608A>T | c.A608T | p.(E203V) | p.(Glu203Val)
c.609G>C or c.609G>T‡ | c.G609C or c.G609T‡ | p.(E203D) | p.(Glu203Asp)
c.611G>T | c.G611T | p.(W204L) | p.(Trp204Leu)
c.613C>A | c.C613A | p.(P205T) | p.(Pro205Thr)
c.613C>T | c.C613T | p.(P205S) | p.(Pro205Ser)
c.614C>T | c.C614T | p.(P205L) | p.(Pro205Leu)
c.619T>C | c.T619C | p.(Y207H) | p.(Tyr207His)
c.620A>C | c.A620C | p.(Y207S) | p.(Tyr207Ser)
c.623T>G | c.T623G | p.(M208R) | p.(Met208Arg)
c.628C>T | c.C628T | p.(P210S) | p.(Pro210Ser)
c.629C>T | c.C629T | p.(P210L) | p.(Pro210Leu)
c.638A>G | c.A638G | p.(K213R) | p.(Lys213Arg)
c.638A>T | c.A638T | p.(K213M) | p.(Lys213Met)
c.640C>T | c.C640T | p.(P214S) | p.(Pro214Ser)
c.641C>T | c.C641T | p.(P214L) | p.(Pro214Leu)
c.643A>G | c.A643G | p.(N215D) | p.(Asn215Asp)
c.644A>G | c.A644G | p.(N215S) | p.(Asn215Ser)
c.[644A>G; 937G>T§]† | c.[A644G; G937T§]† | p.[(N215S; D313Y§)]† | p.[(Asn215Ser; Asp313Tyr§)]†
c.644A>T | c.A644T | p.(N215I) | p.(Asn215Ile)
c.646T>G | c.T646G | p.(Y216D) | p.(Tyr216Asp)
c.647A>G | c.A647G | p.(Y216C) | p.(Tyr216Cys)
c.655A>C | c.A655C | p.(I219L) | p.(Ile219Leu)
c.656T>A | c.T656A | p.(I219N) | p.(Ile219Asn)
c.656T>C | c.T656C | p.(I219T) | p.(Ile219Thr)
c.657C>G | c.C657G | p.(I219M) | p.(Ile219Met)
c.659G>A | c.G659A | p.(R220Q) | p.(Arg220Gln)
c.659G>C | c.G659C | p.(R220P) | p.(Arg220Pro)
c.662A>C | c.A662C | p.(Q221P) | p.(Gln221Pro)
c.664T>G | c.T664G | p.(Y222D) | p.(Tyr222Asp)
c.671A>C | c.A671C | p.(N224T) | p.(Asn224Thr)
c.671A>G | c.A671G | p.(N224S) | p.(Asn224Ser)
c.673C>G | c.C673G | p.(H225D) | p.(His225Asp)
c.682A>C | c.A682C | p.(N228H) | p.(Asn228His)
c.683A>G | c.A683G | p.(N228S) | p.(Asn228Ser)
c.687T>G or c.687T>A‡ | c.T687G or c.T687A‡ | p.(F229L) | p.(Phe229Leu)
c.695T>C | c.T695C | p.(I232T) | p.(Ile232Thr)
c.712A>G | c.A712G | p.(S238G) | p.(Ser238Gly)
c.713G>A | c.G713A | p.(S238N) | p.(Ser238Asn)
c.716T>C | c.T716C | p.(I239T) | p.(Ile239Thr)
c.717A>G | c.A717G | p.(I239M) | p.(Ile239Met)
c.720G>C or c.720G>T‡ | c.G720C or c.G720T‡ | p.(K240N) | p.(Lys240Asn)
c.724A>G | c.A724G | p.(I242V) | p.(Ile242Val)
c.724A>T | c.A724T | p.(I242F) | p.(Ile242Phe)
c.725T>A | c.T725A | p.(I242N) | p.(Ile242Asn)
c.725T>C | c.T725C | p.(I242T) | p.(Ile242Thr)
c.728T>C | c.T728C | p.(L243S) | p.(Leu243Ser)
c.728T>G | c.T728G | p.(L243W) | p.(Leu243Trp)
c.729G>C or c.729G>T‡ | c.G729C or c.G729T‡ | p.(L243F) | p.(Leu243Phe)
c.730G>A | c.G730A | p.(D244N) | p.(Asp244Asn)
c.730G>C | c.G730C | p.(D244H) | p.(Asp244His)
c.733T>G | c.T733G | p.(W245G) | p.(Trp245Gly)
c.740C>G | c.C740G | p.(S247C) | p.(Ser247Cys)
c.747C>G or c.747C>A‡ | c.C747G or c.C747A‡ | p.(N249K) | p.(Asn249Lys)
c.749A>C | c.A749C | p.(Q250P) | p.(Gln250Pro)
c.749A>G | c.A749G | p.(Q250R) | p.(Gln250Arg)
c.750G>C | c.G750C | p.(Q250H) | p.(Gln250His)
c.758T>C | c.T758C | p.(I253T) | p.(Ile253Thr)
c.758T>G | c.T758G | p.(I253S) | p.(Ile253Ser)
c.761_763delTTG | c.761_763delTTG [a.k.a. c.760_762delGTT¶] | p.(V254del) | p.(Val254del)
c.769G>C | c.G769C | p.(A257P) | p.(Ala257Pro)
c.770C>G | c.C770G | p.(A257G) | p.(Ala257Gly)
c.770C>T | c.C770T | p.(A257V) | p.(Ala257Val)
c.772G>C or c.772G>A‡ | c.G772C or c.G772A‡ | p.(G258R) | p.(Gly258Arg)
c.773G>T | c.G773T | p.(G258V) | p.(Gly258Val)
c.776C>A | c.C776A | p.(P259Q) | p.(Pro259Gln)
c.776C>G | c.C776G | p.(P259R) | p.(Pro259Arg)
c.776C>T | c.C776T | p.(P259L) | p.(Pro259Leu)
c.779G>A | c.G779A | p.(G260E) | p.(Gly260Glu)
c.779G>C | c.G779C | p.(G260A) | p.(Gly260Ala)
c.781G>A | c.G781A | p.(G261S) | p.(Gly261Ser)
c.781G>C | c.G781C | p.(G261R) | p.(Gly261Arg)
c.781G>T | c.G781T | p.(G261C) | p.(Gly261Cys)
c.788A>G | c.A788G | p.(N263S) | p.(Asn263Ser)
c.790G>T | c.G790T | p.(D264Y) | p.(Asp264Tyr)
c.794C>T | c.C794T | p.(P265L) | p.(Pro265Leu)
c.800T>C | c.T800C | p.(M267T) | p.(Met267Thr)
c.805G>A | c.G805A | p.(V269M) | p.(Val269Met)
c.805G>C | c.G805C | p.(V269L) | p.(Val269Leu)
c.806T>C | c.T806C | p.(V269A) | p.(Val269Ala)
c.809T>C | c.T809C | p.(I270T) | p.(Ile270Thr)
c.810T>G | c.T810G | p.(I270M) | p.(Ile270Met)
c.811G>A | c.G811A | p.(G271S) | p.(Gly271Ser)
c.[811G>A; 937G>T§]† | c.[G811A; G937T§]† | p.[(G271S; D313Y§)]† | p.[(Gly271Ser; Asp313Tyr§)]†
c.812G>A | c.G812A | p.(G271D) | p.(Gly271Asp)
c.812G>C | c.G812C | p.(G271A) | p.(Gly271Ala)
c.823C>G | c.C823G | p.(L275V) | p.(Leu275Val)
c.827G>A | c.G827A | p.(S276N) | p.(Ser276Asn)
c.829T>G | c.T829G | p.(W277G) | p.(Trp277Gly)
c.831G>C or c.831G>T‡ | c.G831C or c.G831T‡ | p.(W277C) | p.(Trp277Cys)
c.832A>T | c.A832T | p.(N278Y) | p.(Asn278Tyr)
c.835C>G | c.C835G | p.(Q279E) | p.(Gln279Glu)
c.838C>A | c.C838A | p.(Q280K) | p.(Gln280Lys)
c.840A>T or c.840A>C‡ | c.A840T or c.A840C‡ | p.(Q280H) | p.(Gln280His)
c.844A>G | c.A844G | p.(T282A) | p.(Thr282Ala)
c.845C>T | c.C845T | p.(T282I) | p.(Thr282Ile)
c.850A>G | c.A850G | p.(M284V) | p.(Met284Val)
c.851T>C | c.T851C | p.(M284T) | p.(Met284Thr)
c.860G>T | c.G860T | p.(W287L) | p.(Trp287Leu)
c.862G>C | c.G862C | p.(A288P) | p.(Ala288Pro)
c.866T>G | c.T866G | p.(I289S) | p.(Ile289Ser)
c.868A>C or c.868A>T‡ | c.A868C or c.A868T‡ | p.(M290L) | p.(Met290Leu)
c.869T>C | c.T869C | p.(M290T) | p.(Met290Thr)
c.870G>C or c.870G>A‡ or c.870G>T‡ | c.G870C or c.G870A‡ or c.G870T‡ | p.(M290I) | p.(Met290Ile)
c.871G>A | c.G871A | p.(A291T) | p.(Ala291Thr)
c.877C>A | c.C877A | p.(P293T) | p.(Pro293Thr)
c.881T>C | c.T881C | p.(L294S) | p.(Leu294Ser)
c.884T>G | c.T884G | p.(F295C) | p.(Phe295Cys)
c.886A>G | c.A886G | p.(M296V) | p.(Met296Val)
c.886A>C or c.886A>T‡ | c.A886C or c.A886T‡ | p.(M296L) | p.(Met296Leu)
c.887T>C | c.T887C | p.(M296T) | p.(Met296Thr)
c.888G>A or c.888G>T‡ or c.888G>C‡ | c.G888A or c.G888T‡ or c.G888C‡ | p.(M296I) | p.(Met296Ile)
c.893A>G | c.A893G | p.(N298S) | p.(Asn298Ser)
c.897C>G or c.897C>A‡ | c.C897G or c.C897A‡ | p.(D299E) | p.(Asp299Glu)
c.898C>T | c.C898T | p.(L300F) | p.(Leu300Phe)
c.899T>C | c.T899C | p.(L300P) | p.(Leu300Pro)
c.901C>G | c.C901G | p.(R301G) | p.(Arg301Gly)
c.902G>A | c.G902A | p.(R301Q) | p.(Arg301Gln)
c.902G>C | c.G902C | p.(R301P) | p.(Arg301Pro)
c.902G>T | c.G902T | p.(R301L) | p.(Arg301Leu)
c.907A>T | c.A907T | p.(I303F) | p.(Ile303Phe)
c.908T>A | c.T908A | p.(I303N) | p.(Ile303Asn)
c.908T>C | c.T908C | p.(I303T) | p.(Ile303Thr)
c.911G>A | c.G911A | p.(S304N) | p.(Ser304Asn)
c.911G>C | c.G911C | p.(S304T) | p.(Ser304Thr)
c.919G>A | c.G919A | p.(A307T) | p.(Ala307Thr)
c.922A>G | c.A922G | p.(K308E) | p.(Lys308Glu)
c.924A>C or c.924A>T‡ | c.A924C or c.A924T‡ | p.(K308N) | p.(Lys308Asn)
c.925G>C | c.G925C | p.(A309P) | p.(Ala309Pro)
c.926C>T | c.C926T | p.(A309V) | p.(Ala309Val)
c.928C>T | c.C928T | p.(L310F) | p.(Leu310Phe)
c.931C>G | c.C931G | p.(L311V) | p.(Leu311Val)
c.935A>G | c.A935G | p.(Q312R) | p.(Gln312Arg)
c.936G>C or c.936G>T‡ | c.G936C or c.G936T‡ | p.(Q312H) | p.(Gln312His)
c.937G>T§ | c.G937T§ | p.(D313Y§) | p.(Asp313Tyr§)
c.[937G>T§; 1232G>A]† | c.[G937T§; G1232A]† | p.[D313Y§; G411D]† | p.[Asp313Tyr§; Gly411Asp]†
c.938A>G | c.A938G | p.(D313G) | p.(Asp313Gly)
c.946G>A | c.G946A | p.(V316I) | p.(Val316Ile)
c.947T>G | c.T947G | p.(V316G) | p.(Val316Gly)
c.950T>C | c.T950C | p.(I317T) | p.(Ile317Thr)
c.955A>T | c.A955T | p.(I319F) | p.(Ile319Phe)
c.956T>C | c.T956C | p.(I319T) | p.(Ile319Thr)
c.958A>C | c.A958C | p.(N320H) | p.(Asn320His)
c.959A>T | c.A959T | p.(N320I) | p.(Asn320Ile)
c.962A>G | c.A962G | p.(Q321R) | p.(Gln321Arg)
c.962A>T | c.A962T | p.(Q321L) | p.(Gln321Leu)
c.963G>C or c.963G>T‡ | c.G963C or c.G963T‡ | p.(Q321H) | p.(Gln321His)
c.964G>A | c.G964A | p.(D322N) | p.(Asp322Asn)
c.964G>C | c.G964C | p.(D322H) | p.(Asp322His)
c.966C>A or c.966C>G‡ | c.C966A or c.C966G‡ | p.(D322E) | p.(Asp322Glu)
c.967C>A | c.C967A | p.(P323T) | p.(Pro323Thr)
c.968C>G | c.C968G | p.(P323R) | p.(Pro323Arg)
c.973G>A | c.G973A | p.(G325S) | p.(Gly325Ser)
c.973G>C | c.G973C | p.(G325R) | p.(Gly325Arg)
c.978G>C or c.978G>T‡ | c.G978C or c.G978T‡ | p.(K326N) | p.(Lys326Asn)
c.979C>G | c.C979G | p.(Q327E) | p.(Gln327Glu)
c.980A>T | c.A980T | p.(Q327L) | p.(Gln327Leu)
c.983G>C | c.G983C | p.(G328A) | p.(Gly328Ala)
c.989A>G | c.A989G | p.(Q330R) | p.(Gln330Arg)
c.1001G>A | c.G1001A | p.(G334E) | p.(Gly334Glu)
c.1010T>C | c.T1010C | p.(F337S) | p.(Phe337Ser)
c.1012G>A | c.G1012A | p.(E338K) | p.(Glu338Lys)
c.1013A>T | c.A1013T | p.(E338V) | p.(Glu338Val)
c.1016T>A | c.T1016A | p.(V339E) | p.(Val339Glu)
c.1027C>A | c.C1027A | p.(P343T) | p.(Pro343Thr)
c.1028C>T | c.C1028T | p.(P343L) | p.(Pro343Leu)
c.1033T>C | c.T1033C | p.(S345P) | p.(Ser345Pro)
c.1046G>C | c.G1046C | p.(W349S) | p.(Trp349Ser)
c.1055C>G | c.C1055G | p.(A352G) | p.(Ala352Gly)
c.1055C>T | c.C1055T | p.(A352V) | p.(Ala352Val)
c.1061T>A | c.T1061A | p.(I354K) | p.(Ile354Lys)
c.1066C>G | c.C1066G | p.(R356G) | p.(Arg356Gly)
c.1066C>T | c.C1066T | p.(R356W) | p.(Arg356Trp)
c.1067G>A | c.G1067A | p.(R356Q) | p.(Arg356Gln)
c.1067G>C | c.G1067C | p.(R356P) | p.(Arg356Pro)
c.1072G>C | c.G1072C | p.(E358Q) | p.(Glu358Gln)
c.1073A>C | c.A1073C | p.(E358A) | p.(Glu358Ala)
c.1073A>G | c.A1073G | p.(E358G) | p.(Glu358Gly)
c.1074G>T or c.1074G>C‡ | c.G1074T or c.G1074C‡ | p.(E358D) | p.(Glu358Asp)
c.1076T>C | c.T1076C | p.(I359T) | p.(Ile359Thr)
c.1078G>A | c.G1078A | p.(G360S) | p.(Gly360Ser)
c.1078G>C | c.G1078C | p.(G360R) | p.(Gly360Arg)
c.1078G>T | c.G1078T | p.(G360C) | p.(Gly360Cys)
c.1079G>A | c.G1079A | p.(G360D) | p.(Gly360Asp)
c.1082G>A | c.G1082A | p.(G361E) | p.(Gly361Glu)
c.1082G>C | c.G1082C | p.(G361A) | p.(Gly361Ala)
c.1084C>A | c.C1084A | p.(P362T) | p.(Pro362Thr)
c.1085C>T | c.C1085T | p.(P362L) | p.(Pro362Leu)
c.1087C>T | c.C1087T | p.(R363C) | p.(Arg363Cys)
c.1088G>A | c.G1088A | p.(R363H) | p.(Arg363His)
c.1102G>A | c.G1102A | p.(A368T) | p.(Ala368Thr)
c.1117G>A | c.G1117A | p.(G373S) | p.(Gly373Ser)
c.1124G>A | c.G1124A | p.(G375E) | p.(Gly375Glu)
c.1139C>T | c.C1139T | p.(P380L) | p.(Pro380Leu)
c.1153A>G | c.A1153G | p.(T385A) | p.(Tyr385Ala)
c.1163T>A | c.T1163A | p.(L388H) | p.(Leu388His)
c.1168G>A | c.G1168A | p.(V390M) | p.(Val390Met)
c.1172A>C | c.A1172C | p.(K391T) | p.(Lys391Thr)
c.1184G>A | c.G1184A | p.(G395E) | p.(Gly395Glu)
c.1184G>C | c.G1184C | p.(G395A) | p.(Gly395Ala)
c.1192G>A | c.G1192A | p.(E398K) | p.(Glu398Lys)
c.1202_1203insGACTTC | c.1202_1203insGACTTC | p.(T400_S401dup) | p.(Thr400_Ser401dup)
c.1208T>C | c.T1208C | p.(L403S) | p.(Leu403Ser)
c.1225C>A | c.C1225A | p.(P409T) | p.(Pro409Thr)
c.1225C>G | c.C1225G | p.(P409A) | p.(Pro409Ala)
c.1225C>T | c.C1225T | p.(P409S) | p.(Pro409Ser)
c.1228A>G | c.A1228G | p.(T410A) | p.(Thr410Ala)
c.1229C>T | c.C1229T | p.(T410I) | p.(Thr410Ile)
c.1232G>A | c.G1232A | p.(G411D) | p.(Gly411Asp)
c.1234A>C | c.A1234C | p.(T412P) | p.(Thr412Pro)
c.1235C>A | c.C1235A | p.(T412N) | p.(Thr412Asn)
c.1235C>T | c.C1235T | p.(T412I) | p.(Thr412Ile)
c.1253A>G | c.A1253G | p.(E418G) | p.(Glu418Gly)
c.1261A>G | c.A1261G | p.(M421V) | p.(Met421Val)
§ Based on available published data, the GLA variant c.937G>T, (p.(D313Y)) is considered benign (not causing Fabry disease). Consultation with a clinical genetics professional is strongly recommended in patients with Fabry disease who have this GLA variant as additional evaluations may be indicated.
† Multiple variant combination of two or more different variants on a single GLA allele that informs amenability.
‡ Synonymous variants are listed without testing in the in vitro amenability assay. GLA variant(s) with a different nucleotide change affecting the same amino acid position(s) as the tested GLA variant and predicted to encode the same variant alpha-Gal A enzyme are considered synonymous.
¶ c.761_763delTTG has been previously referred to as c.760_762delGTT.

12.2 Pharmacodynamics

In Study 1, 31 of 50 patients with amenable GLA variants (18 on GALAFOLD, 13 on placebo) had lyso‑Gb3 assessments available after 6 months of treatment. The median change from baseline to month 6 in plasma lyso‑Gb3 (nmol/L) was -2.37 (range -69.7, 1.8) in patients on GALAFOLD and 0.53 (range -21.5, 16.3) in patients on placebo. In the open‑label treatment phase of Study 1, the 13 patients who were initially on placebo for 6 months and who switched to GALAFOLD for another 6 months had a median change in lyso‑Gb3 (nmol/L) of -2.72 (range -61.1, -0.3). The 18 patients who were treated with GALAFOLD for 6 months and then continued GALAFOLD in the open‑label treatment phase of Study 1 for an additional 6 months had no further changes in plasma lyso‑Gb3.

In Study 2, 46 of 56 patients with amenable GLA variants (31 on GALAFOLD, 15 on enzyme replacement therapy (ERT)) had lyso‑Gb3 assessments available after 18 months of treatment. The median change from baseline to month 18 in plasma lyso‑Gb3 (nmol/L) was 0.53 (range -2.27, 28.3) in patients on GALAFOLD and -0.03 (range -11.9, 2.57) in patients on ERT.

Cardiac Electrophysiology

At a dose approximately 8 times the recommended dose, GALAFOLD did not prolong the QT interval to any clinically relevant extent.

12.3 Pharmacokinetics

Absorption

Following a single GALAFOLD oral dose of 123 mg, the absolute bioavailability (AUC) of migalastat was approximately 75% and the time to peak plasma concentration (tmax) was approximately 3 hours. Plasma migalastat exposure (AUC0‑∞ and Cmax) demonstrated dose‑proportional increases at oral doses from 75 mg to 1250 mg (doses from 0.5 to 8.3‑fold of the approved recommended dosage). Migalastat does not accumulate following administration of 123 mg GALAFOLD every other day.

Effect of Food: Administration of GALAFOLD one hour before a high‑fat (850 calories; 56% from fat) or light meal (507 calories; 30% from fat), or one hour after a light meal, reduced the mean migalastat AUC0‑∞ by 37% to 42% and Cmax by 15% to 39% compared to the fasting state [see Dosage and Administration (2.2)].

Distribution

The apparent volume of distribution (Vz/F) of migalastat in Fabry patients was approximately 89 L (range: 77 to 133 L) at steady state. There was no detectable plasma protein binding following administration of [^14C]‑migalastat in the concentration range between 1 to 100 microM.

Elimination

Metabolism: Based upon in vivo data, migalastat is a substrate for uridine diphosphate glucuronosyltransferase (UDPGT), a minor elimination pathway.

Excretion: In a mass balance study in healthy male subjects, following oral administration of 123 mg [^14C]‑migalastat, approximately 77% of the total radiolabeled dose was recovered in urine and 20% of the total radiolabeled dose was recovered in feces with an overall total recovery of 98% within 96 hours post‑dose. In urine, unchanged migalastat accounted for 80% of the radioactivity, which equates to 62% of the administered dose. In feces, unchanged migalastat was the only drug‑related component. In plasma, unchanged migalastat accounted for approximately 77% of the plasma radioactivity and three dehydrogenated O‑glucuronide conjugated metabolites, M1 to M3, together accounted for approximately 13% of the plasma radioactivity, none of which comprised more than 6% of the radiolabeled dose. Approximately 9% of the total radioactivity in plasma was unassigned.

Following a single oral dose of 123 mg GALAFOLD, migalastat is cleared from plasma with a mean half‑life (t½) of approximately 4 hours and apparent clearance of 12.5 L/hr.

Specific Populations

Male and Female Patients: The pharmacokinetic characteristics of migalastat were not significantly different between healthy male and female subjects or patients with Fabry disease.

Racial or Ethnic Groups: Clinical data indicate no ethnic differences in patient populations studied with migalastat.

Patients with Renal Impairment: In a single‑dose study in subjects with varying degrees of renal impairment, exposure to migalastat (AUC) was increased by 1.2-, 1.8-, and 4.3-fold in subjects with mild (eGFR 60 to 90 mL/min/1.73 m^2), moderate (eGFR 30 to 59 mL/min/1.73 m^2), and severe renal impairment (eGFR less than 30 mL/min/1.73 m^2), respectively, while the Cmax remained unchanged with severity of renal impairment [see Use in Specific Populations (8.6)].

Drug Interaction Studies

In Vitro Studies
Migalastat is not a known inhibitor or inducer of cytochrome P450 (CYP450) enzymes, nor is it an inhibitor of BCRP, MDR1, P‑glycoprotein (P‑gp), or BSEP human efflux transporters, or OATP1B1, OATP1B3, OAT1, OAT3, OCT1, OCT2, MATE1, or MATE2‑K human uptake transporters. Migalastat is not a substrate of P‑gp, BCRP, MDR1 or MATE1, MATE2‑K, OAT1, OAT3, or OCT2. Migalastat showed low affinity for SGLT1, as both a substrate and an inhibitor, and showed no activity for SGLT2.

Clinical Studies: Effects of other Drugs on Migalastat
Co‑administration of 190 mg caffeine reduced the mean migalastat AUC0‑∞ by 55% and Cmax by 60% compared to without caffeine co‑administration. The tmax of migalastat was not affected by co‑administration of caffeine. No clinically significant pharmacokinetic changes were observed for migalastat when co‑administered with sucrose, aspartame or acesulfame potassium [see Dosage and Administration (2.2) and Drug Interactions (7.1)].

13 NONCLINICAL TOXICOLOGY

13.1 Carcinogenesis, Mutagenesis, Impairment of Fertility

Carcinogenesis

The carcinogenic potential of migalastat was assessed in a 2‑year study in rats and a 26‑week study in Tg.rasH2 mice. In the 2‑year rat study, migalastat was not tumorigenic at oral doses of up to 600 mg/kg twice daily (24 times the recommended dose based on AUC). In the 26‑week study in Tg.rasH2 mice, migalastat was not tumorigenic at oral doses of up to 1000 mg/kg/day in males and 500 mg/kg/day in females.

Mutagenesis

Migalastat was negative in the bacterial mutagenicity (Ames) assay, in vitro cell mutation assay in L5178Y mouse lymphoma TK+/- cells, and in vivo micronucleus assay in rats.

Impairment of Fertility

Oral administration of up to 12.5 mg/kg migalastat twice daily in rats (equivalent to the human AUC at the recommended dose) produced a significant decrease in male fertility. This effect was completely reversed after four weeks of recovery. Female fertility was not affected.

14 CLINICAL STUDIES

Study AT1001‑011 (referred to as Study 1; NCT00925301) included a 6‑month randomized, double‑blind, placebo‑controlled phase followed by a 6‑month open‑label treatment phase and a 12‑month open‑label extension phase. Patients received 123 mg GALAFOLD orally every other day taken without consuming food 2 hours before and 2 hours after each dose to give a minimum 4‑hour fast [see Dosage and Administration (2.2)].

A total of 67 patients with Fabry disease who were naïve to GALAFOLD and enzyme replacement therapy (ERT) or were previously treated with ERT (agalsidase beta or non‑U.S. approved agalsidase alfa) and had been off ERT for at least 6 months were randomized in a 1:1 ratio to receive either GALAFOLD 123 mg every other day or placebo for the first 6 months. In the second 6 months, all patients were treated with GALAFOLD.

Results - Patients with Fabry Disease with Amenable GLA Variants

Of the 67 enrolled patients, 50 patients (32 females, 18 males) had amenable GLA variants based on the in vitro amenability assay [see Clinical Pharmacology (12.1)]. The median age of this population was 45 years (range from 16 to 68 years old); 65 were White (97%), and 2 were other racial group (3%). The major efficacy outcome measure of the average number of GL‑3 inclusions per kidney interstitial capillary (KIC) in renal biopsy samples was assessed by light microscopy before and after treatment.

Efficacy was evaluated after 6 months of treatment in 45 of 50 patients with amenable GLA variants (29 females and 16 males) and with available histology data both at baseline and month 6. Of the 45 evaluable patients, 25 received GALAFOLD (18 females, 7 males) and 20 received placebo (11 females, 9 males). The proportion of patients with ≥ 50% reduction from baseline in the average number of GL‑3 inclusions per KIC and the median changes from baseline in the average number of GL‑3 inclusions per KIC after 6 months of treatment in Study 1 are shown in Table 3.

Table 3: Changes from Baseline to Month 6 in Average Number of GL‑3 Inclusions per KIC in Adults with Fabry Disease with Amenable GLA Variants in Study 1 (N = 45)
 | GALAFOLD n/N (%) with ≥ 50% reduction Median change from baseline (range) | Placebo n/N (%) with ≥ 50% reduction Median change from baseline (range)
All patients (N = 45) | 13/25 (52%) -0.04 (-1.94, 0.26) | 9/20 (45%) -0.03 (-1.00, 1.69)
Females (N = 29) | 8/18 (44%) -0.02 (-0.46, 0.26) | 5/11 (46%) -0.03 (-0.35, 0.10)
Males (N = 16) | 5/7 (71%) -1.10 (-1.94, -0.02) | 4/9 (44%) -0.03 (-1.00, 1.69)
Patients with baseline GL-3 ≥ 0.3 (N = 17; 9 males, 8 females) | 7/9 (78%) -0.91 (-1.94, 0.19) | 2/8 (25%) -0.02 (-1.00, 1.69)
Patients with baseline GL-3 < 0.3 (N = 28; 7 males, 21 females) | 6/16 (38%) -0.02 (-0.10, 0.26) | 7/12 (58%) -0.05 (-0.16, 0.14)

Results - Patients with Fabry Disease with Non‑Amenable GLA Variants

Of the 67 enrolled patients in Study 1, 17 patients had non‑amenable GLA variants. These patients had no change from baseline in the average number of GL‑3 inclusions per KIC after 6 months of treatment.

16 HOW SUPPLIED/STORAGE AND HANDLING

GALAFOLD capsules are supplied as 123 mg migalastat, size “2” capsules with an opaque blue cap and opaque white body filled with white to pale brown powder and imprinted with “A1001” in black ink.

GALAFOLD capsules are packaged as two 7‑count capsules blister strips with aluminum foil lidding encased in cardboard blister cards providing 14 capsules per wallet pack that supplies the drug product for 4 weeks (28 days).

Wallet pack containing 14 GALAFOLD capsules NDC 71904‑100‑01.

Store at USP Controlled Room Temperature of 20° to 25°C (68° to 77°F). Excursions are permitted between 15° to 30°C (59° to 86°F).

Store in the original packaging to protect from moisture.

17 PATIENT COUNSELING INFORMATION

Advise the patient to read the FDA‑approved patient labeling (Patient Information and Instructions for Use).

Administration

Advise the patient:

- To take GALAFOLD once every other day at the same time of day and do not take on consecutive days [see Dosage and Administration (2.2)].
- Swallow capsule whole. Do not cut, crush, or chew the capsule [see Dosage and Administration (2.2)].
- Take GALAFOLD on an empty stomach. Do not consume food or caffeine at least 2 hours prior to and 2 hours after taking GALAFOLD to give a minimum 4 hour fast [see Dosage and Administration (2.2)].
- Water (plain, flavored, or sweetened), fruit juices without pulp, and caffeine‑free carbonated beverages can be consumed during the fasting period [see Dosage and Administration (2.2)].
- If the GALAFOLD dose is missed, take the missed dose if it is within 12 hours of the time that the dose should have been taken. If more than 12 hours have passed, take GALAFOLD at the next planned dosing day and time following the original every‑other‑day dosing schedule [see Dosage and Administration (2.3)].
- To inform the healthcare provider of all medicines the patient takes, including prescription and over‑the‑counter medicines, vitamins, and herbal supplements [see Drug Interactions (7.1)].

Pregnancy and Lactation Study

Inform the patient and/or caregiver that there is a study that collects data on pregnant women with Fabry disease, and data on the effects of GALAFOLD on lactation in women with Fabry disease and their neonates and infants up to 1 year of age who are exposed through breast milk. Encourage the patient and/or caregiver to participate and state that participation is voluntary [see Use in Specific Populations (8.1)].

Manufactured for:
Amicus Therapeutics US, LLC
3675 Market Street
Philadelphia, PA 19104

GALAFOLD is a registered trademark of Amicus Therapeutics, Inc.

PATIENT INFORMATION

GALAFOLD® (GAL-a-fold)
(migalastat)
capsules

What is GALAFOLD?

GALAFOLD is a prescription medicine used to treat adults with Fabry disease who have a certain genetic change (variant) in the galactosidase alpha gene (GLA) that is responsive (amenable) to GALAFOLD.
It is not known if GALAFOLD is safe and effective in children.

Before taking GALAFOLD, tell your healthcare provider about all of your medical conditions, including if you:

- have kidney problems.
- are pregnant or plan to become pregnant. It is not known if GALAFOLD will harm your unborn baby.
- are breastfeeding or plan to breastfeed. GALAFOLD may pass into your breast milk. Talk to your healthcare provider about the best way to feed your baby if you take GALAFOLD.

Pregnancy and Breastfeeding Exposure Study. There is a study that collects information on pregnant women with Fabry disease and women with Fabry disease who take GALAFOLD and breastfeed a baby up to 1 year of age. The purpose of this study is to collect information about the health of you and your baby. Talk to your healthcare provider about how you can take part in this study.

Tell your healthcare provider about all the medicines you take, including prescription and over-the-counter medicines, vitamins, and herbal supplements. Especially tell your healthcare provider if you take medicines or supplements containing caffeine as these medicines or supplements may affect how GALAFOLD works.

Know the medicines you take. Keep a list of them and show it to your healthcare provider and pharmacist each time you get a new medicine.

How should I take GALAFOLD?

- Read the Instructions for Use at the end of this Patient Information leaflet for detailed instructions about the right way to take GALAFOLD.
- Take 1 GALAFOLD capsule every other day at the same time of day. Do not take GALAFOLD two days in a row.
- Swallow the GALAFOLD capsule whole. Do not cut, crush, or chew the GALAFOLD capsule.
- Take GALAFOLD on an empty stomach.
- Do not eat food, or take or drink any product that contains caffeine at least 2 hours before and 2 hours after taking GALAFOLD to give a minimum 4 hour fast.
- You may drink water (plain, flavored, or sweetened), fruit juices without pulp, and caffeine-free carbonated beverages during this time when you cannot eat.
- If you miss a dose of GALAFOLD, take the missed dose of GALAFOLD within 12 hours of your normal schedule. If more than 12 hours have passed, do not make up the missed dose. Take your next dose of GALAFOLD at your next scheduled day and time following your original every-other-day dosing schedule.
  - For example, if you miss a dose that you would normally take at 8:00 AM, then you should take that dose before 8:00 PM on the same day. If you do not take the missed dose before 8:00 PM on the same day, you should take your next dose at 8:00 AM on your next scheduled dosing day.

What are the possible side effects of GALAFOLD?

The most common side effects of GALAFOLD include:
• headache
• stuffy or runny nose and sore throat
• urinary tract infection
• nausea
• fever

These are not all the possible side effects of GALAFOLD.
Call your doctor for medical advice about side effects. You may report side effects to FDA at 1-800-FDA-1088.
You may also report side effects to Amicus Therapeutics at 1-877-426-4287.

How should I store GALAFOLD?
• Store GALAFOLD at room temperature between 68°F to 77°F (20°C to 25°C).
• Keep GALAFOLD capsules in the blister card they come in to protect from moisture.
Keep GALAFOLD and all medicines out of the reach of children.

General information about the safe and effective use of GALAFOLD.

Medicines are sometimes prescribed for purposes other than those listed in a Patient Information leaflet. Do not use GALAFOLD for a condition for which it was not prescribed. Do not give GALAFOLD to other people, even if they have the same symptoms that you have. It may harm them. You can ask your pharmacist or healthcare provider for information about GALAFOLD that is written for health professionals.

What are the ingredients in GALAFOLD?

Active ingredient: migalastat hydrochloride

Inactive ingredients: magnesium stearate and pregelatinized starch.
Capsule shells contain gelatin, indigotine - FD&C Blue 2, and titanium dioxide.
The black ink contains black iron oxide, potassium hydroxide, and shellac.

Manufactured for: Amicus Therapeutics US, LLC, 3675 Market Street, Philadelphia, PA 19104

GALAFOLD is a registered trademark of Amicus Therapeutics, Inc.

For more information, go to www.GALAFOLD.com or call 1-877-426-4287.

This Patient Information has been approved by the U.S. Food and Drug Administration.

Revised: June 2023

INSTRUCTIONS FOR USE
GALAFOLD® (GAL-a-fold)
(migalastat)
capsules

This Instructions for Use contains information on how to take GALAFOLD. Read this Instructions for Use before you start taking GALAFOLD and each time you get a refill. There may be new information. This information does not take the place of talking to your healthcare provider about your medical condition or treatment.

Important Information You Need to Know Before Taking GALAFOLD.

- Take 1 GALAFOLD capsule every other day at the same time of day. Do not take GALAFOLD two days in a row.
- Swallow the GALAFOLD capsule whole. Do not cut, crush, or chew the GALAFOLD capsule.
- Take GALAFOLD on an empty stomach.
- Do not eat food, or take or drink any product that contains caffeine at least 2 hours before and 2 hours after taking GALAFOLD to give a minimum 4 hour fast.
- You may drink water (plain, flavored, or sweetened), fruit juices without pulp, and caffeine-free carbonated beverages during this time when you cannot eat.

How to remove a capsule:

Figure A

Step 1. Remove the adhesive seal holding the cover.
Lift the cover of your GALAFOLD carton (See Figure A).

Figure B. Opened carton

Step 2. Press and hold down the purple tab with your thumb on the left side of the carton (See Figure B), and continue to Step 3.

Figure C

Step 3. Grasp the tab on the right side of the blister card where it says, “PULL OUT HERE” and pull out the folded blister card (See Figure C).

Figure D. Front of the blister card

Step 4. Unfold the blister card (See Figure D).

Taking GALAFOLD capsules:

Each GALAFOLD blister card contains 14 GALAFOLD capsules (enough for 28 days of treatment with GALAFOLD) and 14 white cardboard circles. The white cardboard circles are to remind you to take GALAFOLD every other day.

The arrow directs you to begin the next 2 weeks of treatment after Day 14 (See Figure E).

Figure E. Front of the blister card

Figure F. Front of the blister card

Step 5. On your first day of taking GALAFOLD from a new blister card, record the date on the blister card next to “Starting date:” (See Figure F).

Figure G. Back of the blister card

Step 6. Locate the GALAFOLD capsule to remove for the dosing day.

Turn the blister card over to show the back of the card.

Bend the card as shown (See Figure G).

Note: Bending the blister card helps raise the oval perforated cardboard.

Figure H. Back of the blister card

Step 7. Remove the oval perforated cardboard (See Figure H).
Note: After removing the oval cardboard, the white backing of the foil may be present, which is ok.

Figure I. Front of the blister card

Step 8. Turn the blister card over to show the front of the card.
Push the GALAFOLD capsule out (See Figure I).

Figure J. Front of the blister card

Step 9. On the next day, move to the perforated white cardboard circle on the top row.
Press down on the white cardboard circle to remove it (See Figure J).
Note: Removing this white cardboard circle will help you remember which day you do not take GALAFOLD.
Take 1 GALAFOLD capsule every other day.
Fold the blister card, and slide it back into the carton after each use.

Change (alternate) each day between taking the GALAFOLD capsule and removing the perforated white cardboard circle until you reach Day 28. Start a new blister card when you are finished with Day 28.

How should I store GALAFOLD?
• Store GALAFOLD at room temperature between 68°F to 77°F (20°C to 25°C).
• Keep GALAFOLD capsules in the blister card they come in to protect from moisture.
Keep GALAFOLD and all medicines out of the reach of children.

Manufactured for:
Amicus Therapeutics US, LLC
3675 Market Street
Philadelphia, PA 19104

GALAFOLD is a registered trademark of Amicus Therapeutics, Inc.

This Instructions for Use has been approved by the U.S. Food and Drug Administration.

Revised: June 2023